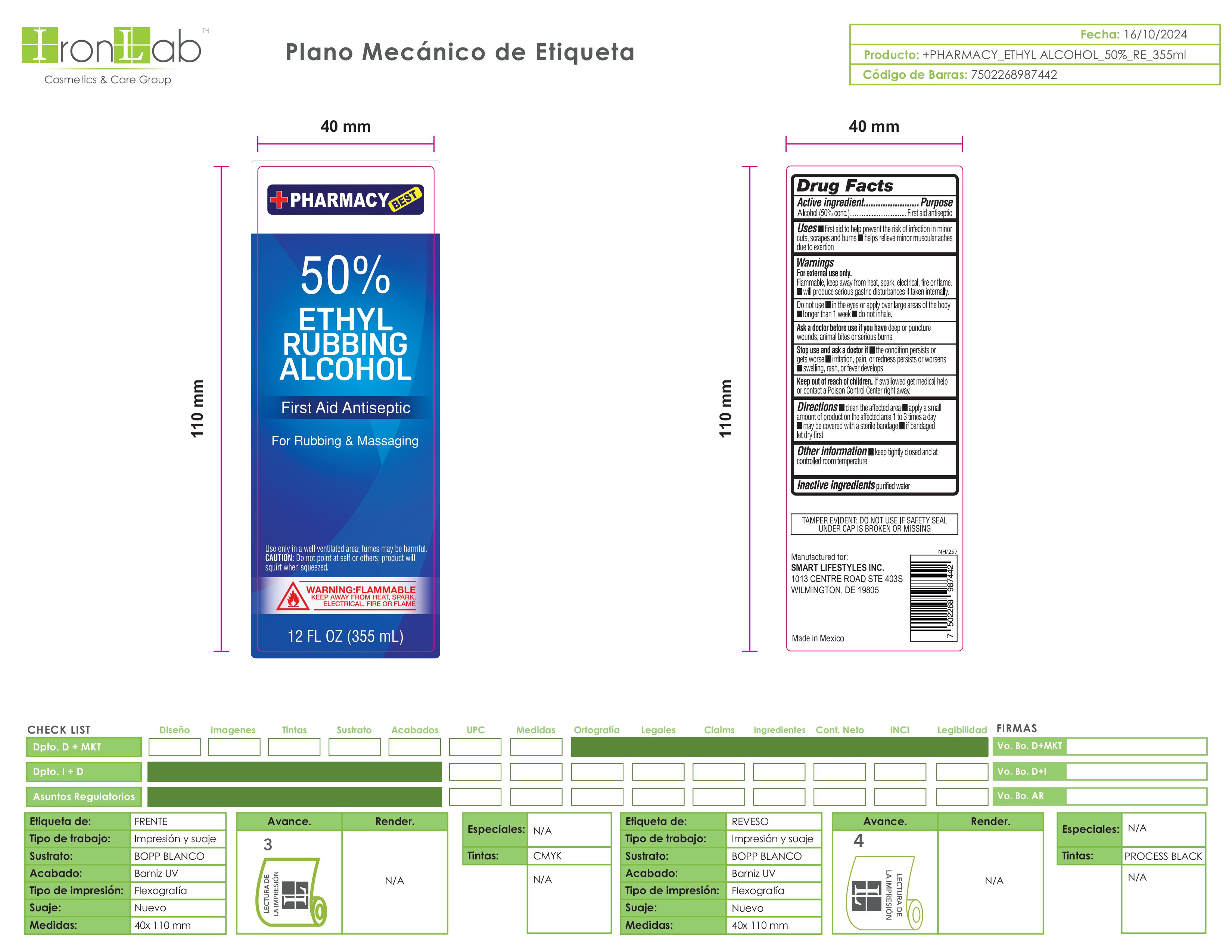 DRUG LABEL: 50 Ethyl Rubbing Alcohol
NDC: 74375-030 | Form: LIQUID
Manufacturer: Iron Lab SA de CV
Category: otc | Type: HUMAN OTC DRUG LABEL
Date: 20260217

ACTIVE INGREDIENTS: ALCOHOL 50 mL/100 mL
INACTIVE INGREDIENTS: WATER

50 Ethyl Rubbing Alcohol Iron Lab SA de CV

DOSAGE AND ADMINISTRATION

To decrease bacteria on the skin that could cause disease. Recommended for repeated use.

INACTIVE INGREDIENT

Purified Water

WARNINGS

For external use only: hands. Flammable, Keep away from fire of flame.

OTHER SAFETY INFORMATION

Store below 105°F. May discolor some fabrics. Harmful to wood finishes and plastic

DOSAGE AND ADMINISTRATION

Thoroughly cover your hands with product and allow to dry without wiping. Children under 6 years of age should be supervised when using this product. Not recommended for infants.

PURPOSE

Antiseptic Alcohol

KEEP OUT OF REACH OF CHILDREN

If swallowed, get medical help or contact a Poison Control Center right away

ASK DOCTOR

Irritation or redness develops. Condition persist for more than 72 hours.

ACTIVE INGREDIENT

50% Etyhl Alcohol

INDICATIONS AND USAGE

To decrease bacteria on the skin that could cause disease. Recommended for repeated use

PACKAGE LABEL

Ethyl Rubbing Alcohol 50%